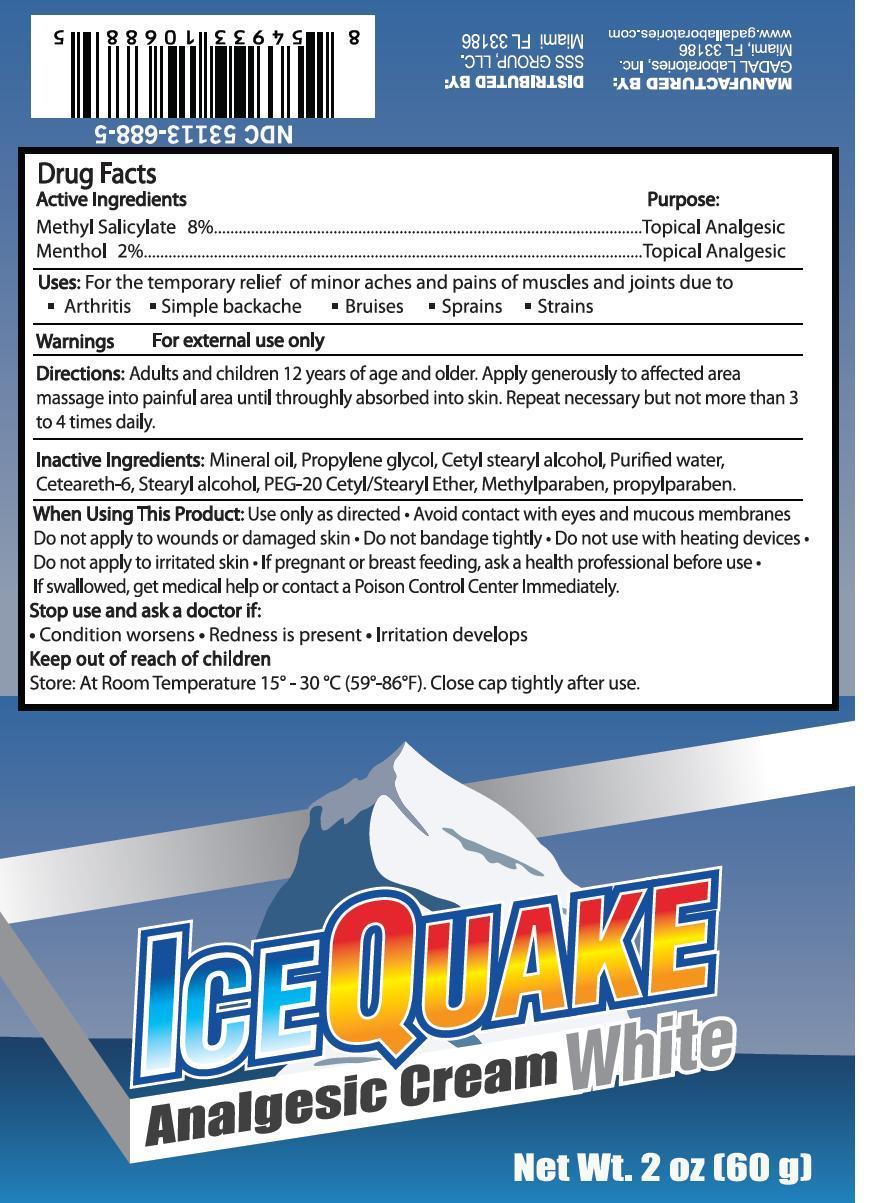 DRUG LABEL: Ice Quake
NDC: 53113-688 | Form: CREAM
Manufacturer: Gadal Laboratories Inc
Category: otc | Type: HUMAN OTC DRUG LABEL
Date: 20130920

ACTIVE INGREDIENTS: MENTHOL 2 g/100 g; METHYL SALICYLATE 8 g/100 g
INACTIVE INGREDIENTS: MINERAL OIL; PROPYLENE GLYCOL; CETOSTEARYL ALCOHOL; WATER; CETEARETH-6; STEARYL ALCOHOL; POLYOXYL 20 CETOSTEARYL ETHER; METHYLPARABEN; PROPYLPARABEN

Active Ingredients Purpose

Methyl Salicylate 8% Topical Analgesic

Menthol 2% Topical Analgesic

Purpose

Topical Analgesic

Uses

For the temporary relief of minor aches and pains of muscles and joints due to

- arthritis
- simple backache
- strains
- bruises
- sprains

Warnings

For external use only

When using this product: Use only as directed

- avoid contact with the eyes and mucous membranes
- do not bandage tightly
- do not apply to wounds or damaged skin
- do not use with heating devices
- do not apply to irritated skin
- if pregnant or breast feeding, ask a health prodessional before us

Stop use and ask a doctor if

- condition worsens
- redness is present
- irritation develops

Keep out of reach of children. If swallowed get medical help or contact a Poison Control Center immediately.

Directions

- adults and children 2 years of age and older; apply generously to affected area massage into painful area until thoroughly absorbed into skin. Repeat if necessary but not more than 3 to 4 times daily.

INACTIVE INGREDIENT

Inactive ingredients: mineral oil, propylene glycol, cetyl stearyl alcohol, purified water, ceteareth-6, stearyl alcohol, PEG-20 Cetyl/stearyl ether, methylparaben, propylparaben

QUESTIONS

SSS Group, LLC Miami, Fl 33183